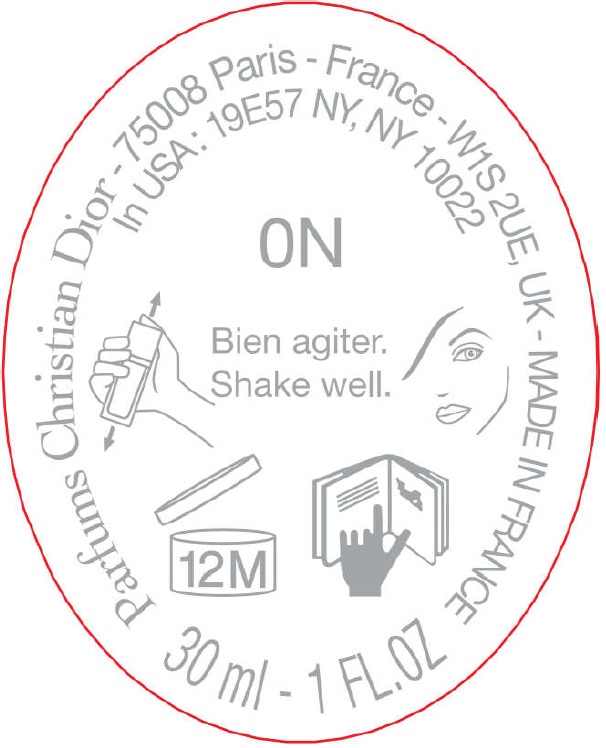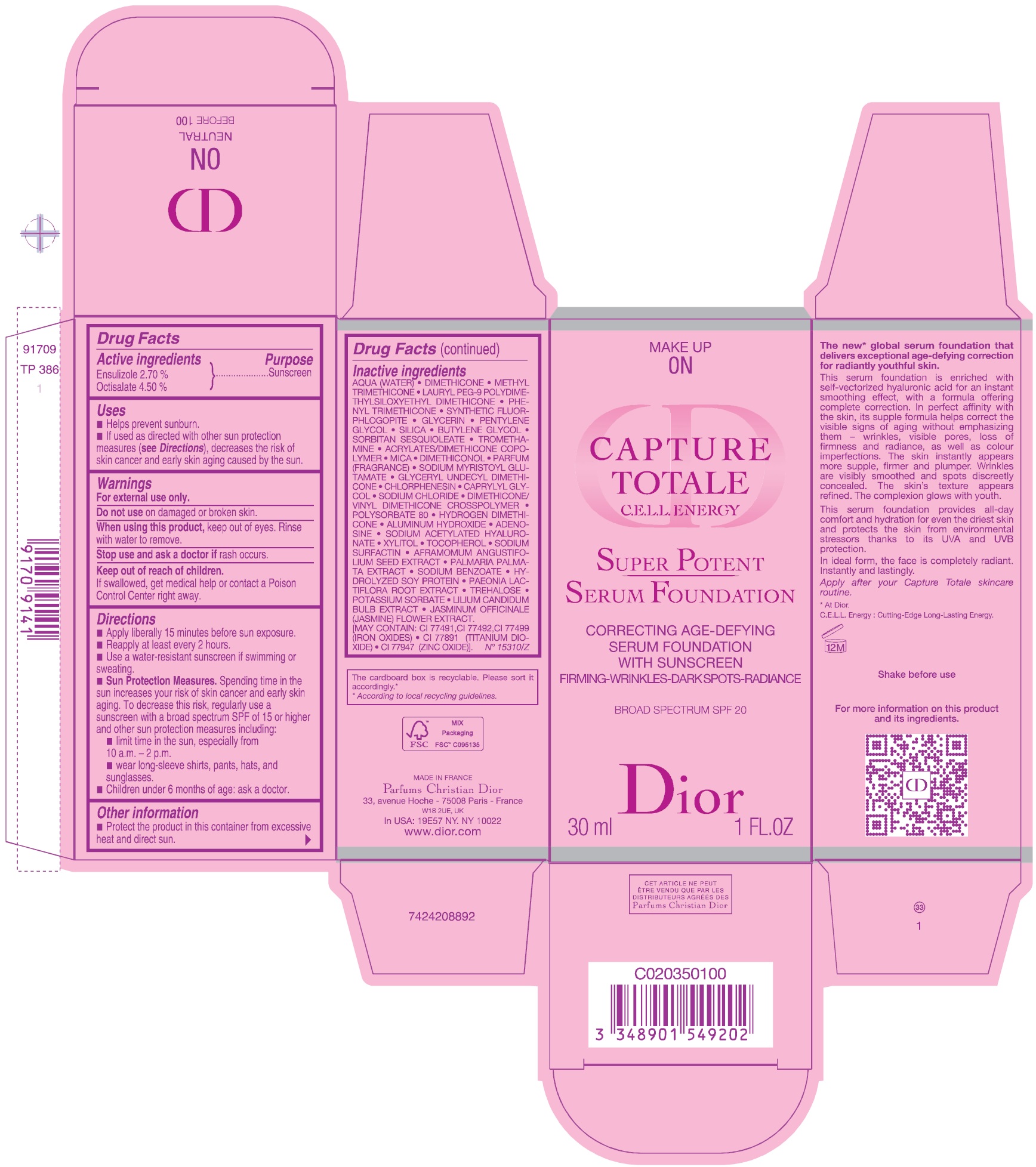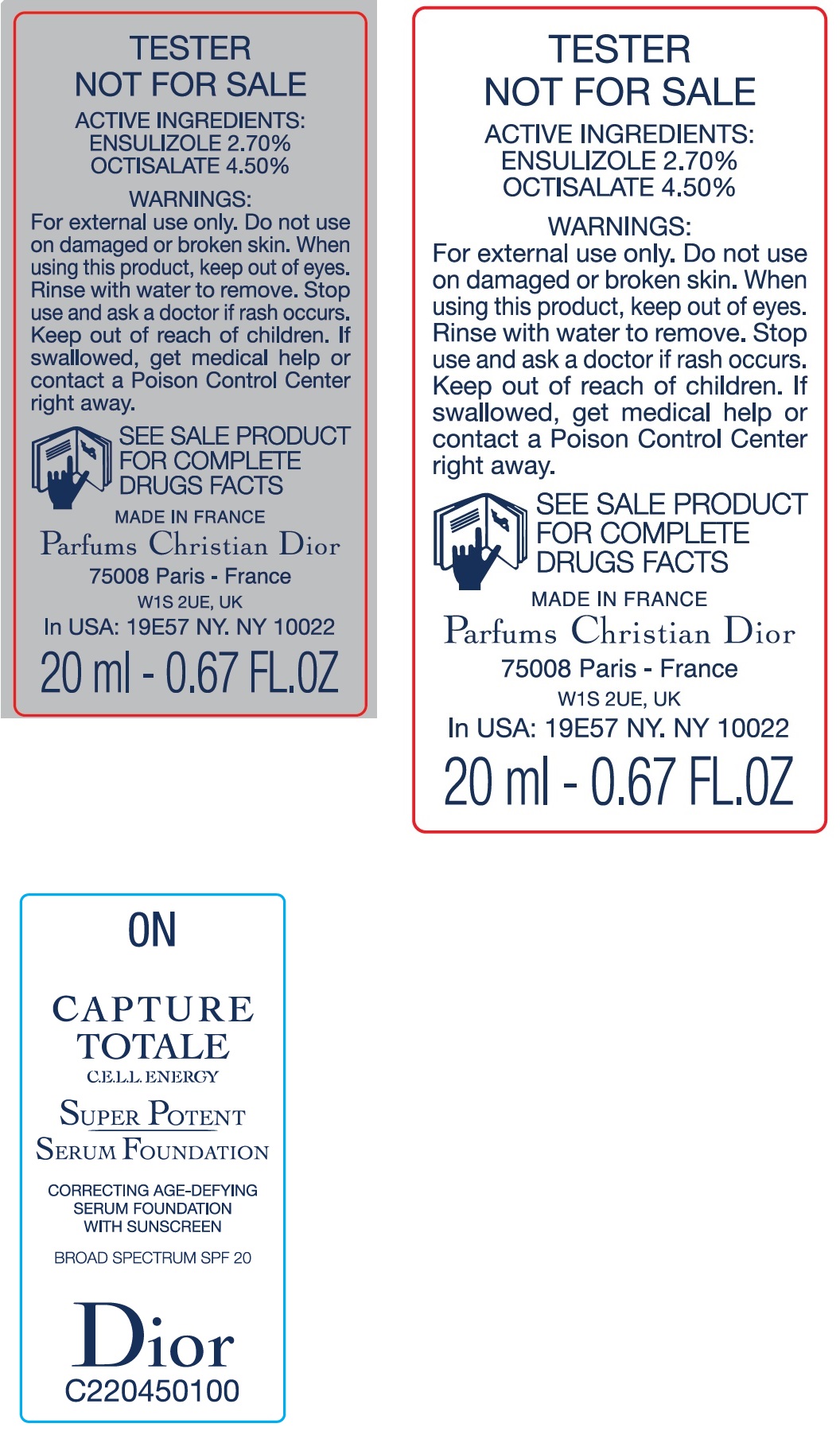 DRUG LABEL: CAPTURE TOTALE C.E.L.L. ENERGY SUPER POTENT SERUM FOUNDATION BROAD SPECTRUM SPF 20 0N
NDC: 61957-2400 | Form: EMULSION
Manufacturer: Parfums Christian Dior
Category: otc | Type: HUMAN OTC DRUG LABEL
Date: 20251217

ACTIVE INGREDIENTS: ENSULIZOLE 27 mg/1 mL; OCTISALATE 45 mg/1 mL
INACTIVE INGREDIENTS: DIMETHICONE; METHYL TRIMETHICONE; LAURYL PEG-9 POLYDIMETHYLSILOXYETHYL DIMETHICONE; PHENYL TRIMETHICONE; MAGNESIUM POTASSIUM ALUMINOSILICATE FLUORIDE; GLYCERIN; PENTYLENE GLYCOL; SILICON DIOXIDE; BUTYLENE GLYCOL; WATER; SORBITAN SESQUIOLEATE; TROMETHAMINE; MICA; DIMETHICONOL (100000 CST); SODIUM MYRISTOYL GLUTAMATE; CHLORPHENESIN; CAPRYLYL GLYCOL; SODIUM CHLORIDE; DIMETHICONE/VINYL DIMETHICONE CROSSPOLYMER (HARD PARTICLE); POLYSORBATE 80; HYDROGEN DIMETHICONE (13 CST); ALUMINUM HYDROXIDE; ADENOSINE; SODIUM ACETYLATED HYALURONATE; XYLITOL; TOCOPHEROL; AFRAMOMUM ANGUSTIFOLIUM SEED; PALMARIA PALMATA; SODIUM BENZOATE; HYDROLYZED SOY PROTEIN (ENZYMATIC; 2000 MW); PAEONIA LACTIFLORA ROOT; JASMINUM OFFICINALE FLOWER

CAPTURE TOTALE C.E.L.L. ENERGY SUPER POTENT SERUM FOUNDATION BROAD SPECTRUM SPF 20 0N

Active ingredients

Ensulizole 2.70 % Octisalate 4.50 %

Purpose

Sunscreen

Uses

- Helps prevent sunburn.
- If used as directed with other sun protection measures (), decreases the risk of skin cancer and early skin aging caused by the sun. see Directions

Warnings

For external use only.

Do not use

on damaged or broken skin.

When using this product,

keep out of eyes. Rinse with water to remove.

Stop use and ask a doctor if

rash occurs.

Keep out of reach of children.

If swallowed, get medical help or contact a Poison Control Center right away.

Directions

- Apply liberally 15 minutes before sun exposure.
- Reapply at least every 2 hours.
- Use a water-resistant sunscreen if swimming or sweating.
- Spending time in the sun increases your risk of skin cancer and early skin aging. To decrease this risk, regularly use a sunscreen with a broad spectrum SPF of 15 or higher and other sun protection measures including: Sun Protection Measures.
- limit time in the sun, especially from 10 a.m. - 2 p.m.
- wear long-sleeve shirts, pants, hats, and sunglasses.
- Children under 6 months of age: ask a doctor.

Other information

- Protect the product in this container from excessive heat and direct sun.

Inactive ingredients

• AQUA (WATER) • DIMETHICONE • METHYL TRIMETHICONE • LAURYL PEG-9 POLYDIMETHYLSILOXYETHYL DIMETHICONE • PHENYL TRIMETHICONE • SYNTHETIC FLUOROPHLOGOPITE • GLYCERIN • PENTYLENE GLYCOL • SILICA • BUTYLENE GLYCOL• SORBITAN SESQUIOLEATE • TROMETHAMINE • ACRYLATES/DIMETHICONE COPOLYMER • MICA • DIMETHICONOL • PARFUM (FRAGRANCE) • SODIUM MYRISTOYL GLUTAMAT • GLYCERYL UNDECYL DIMETHICONE • CHLORPHENESIN • CAPRYLYL GLYCOL• SODIUM CHLORIDE • DIMETHICONE/VINYL DIMETHICONE CROSSPOLYMER • POLYSORBATE 80 • HYDROGEN DIMETHICONE • ALUMINUM HYDROXIDE • ADENOSINE• SODIUM ACETYLATED HYALURONATE • XYLITOL • TOCOPHEROL • SODIUM SURFACTIN • AFRAMOMUM ANGUSTIFOLIUM SEED EXTRACT • PALMARIA PALMATA EXTRACT • SODIUM BENZOATE • HYDROLYZED SOY PROTEIN • PAEONIA LACTIFLORA ROOT EXTRACT • JASMINUM OFFICINALE (JASMINE) FLOWER EXTRACT. [MAY CONTAIN:CI 77491,CI 77492,CI 77499 (IRON OXIDES) • CI 77891 (TITANIUM DIOXIDE) • CI 77947 (ZINC OXIDE)].
N°15310/Z